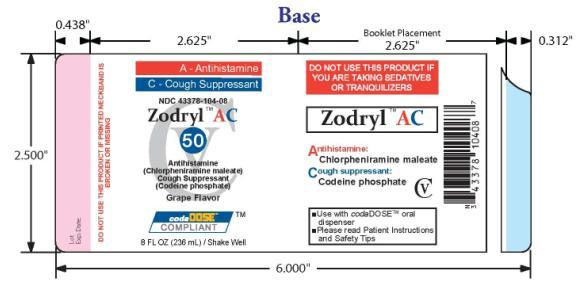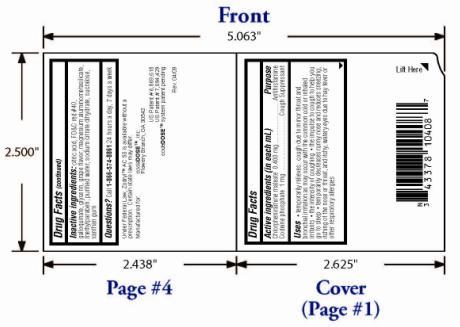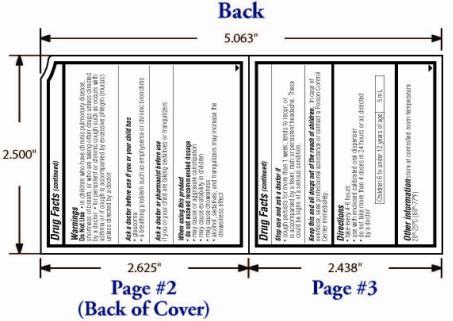 DRUG LABEL: Zodryl AC 50
NDC: 43378-104 | Form: SUSPENSION
Manufacturer: CodaDose, Inc.
Category: otc | Type: HUMAN OTC DRUG LABEL
Date: 20090824
DEA Schedule: CV

ACTIVE INGREDIENTS: CHLORPHENIRAMINE MALEATE 2 mg/5 mL; CODEINE PHOSPHATE 5 mg/5 mL
INACTIVE INGREDIENTS: ANHYDROUS CITRIC ACID; FD&C RED NO. 40; TANNIC ACID; GLYCERIN; MAGNESIUM ALUMINUM SILICATE; METHYLPARABEN; WATER; SODIUM CITRATE; SUCRALOSE; XANTHAN GUM

ZODRYL AC 50 – chlorpheniramine maleate and codeine phosphate suspension

OTC - ACTIVE INGREDIENT

Chlorpheniramine maleate 0.400 mg/1mL: antihistamine; Codeine phosphate 1 mg/1mL: cough suppressant

OTC - PURPOSE

Temporarily relieves: cough due to minor throat and bronchial irritation as may occur with the common cold or inhaled irritants; the intensity of coughing; the impulse to cough to help you go to sleep; temporarily decreases runny nose and reduces sneezing, itching of the nose or throat, and itchy, watery eyes due to hay fever or other upper respiratory allergies

Warnings

OTC - DO NOT USE

in children who have chronic pulmonary disease, shortness of breath, or who are taking other drugs unless directed by a doctor; for persistent or chronic cough such as occurs with asthma or if cough is accompanied by excessive phlegm (mucus) unless directed by a doctor

OTC - ASK DOCTOR

before use if you or your child has glaucoma; a breathing problem such as emphysema or chronic bronchitis

OTC - ASK DOCTOR/PHARMACIST

if you or your child are taking sedatives or tranquilizers

OTC - WHEN USING

do not exceed recommended dosage; may cause or aggravate constipation; may cause excitability in children; may cause drowsiness; alcohol, sedatives, and tranquilizers may increase the drowsiness effect

OTC - STOP USE

cough persists for more than 1 week, tends to recur, or is accompanied by a fever, rash, or persistent headache. These could be signs of a serious condition.

OTC - KEEP OUT OF REACH OF CHILDREN

In case of overdose, seek professional assistance for contact a Poison Control Center immediately.

Directions:

- Take every 4-6 hours
- Use only with enclosed calibrated oral dispenser
- Do not take more than 4 doses in 24 hours or as directed by a doctor

Children 6 to under 12 years of age: 5mL

Other information store at controlled room temperature 20°-25°C (68°-77°F).

INACTIVE INGREDIENT

Citric acid, FD&C red #40, galloquinate, glycerin, grape flavor, magnesium aluminometasilicate, methylparaben, purified water, sodium citrate dihydrate, sucralose, xanthan gum

OTC - QUESTIONS

Call 1-866-574-8861 24 hours a day, 7 days a week.

PACKAGE LABEL.PRINCIPAL DISPLAY PANEL

Figure 1. Primary Label- Front Page
Figure 2. Primary Label – Second Page
Figure 3. Primary Label – Last Page